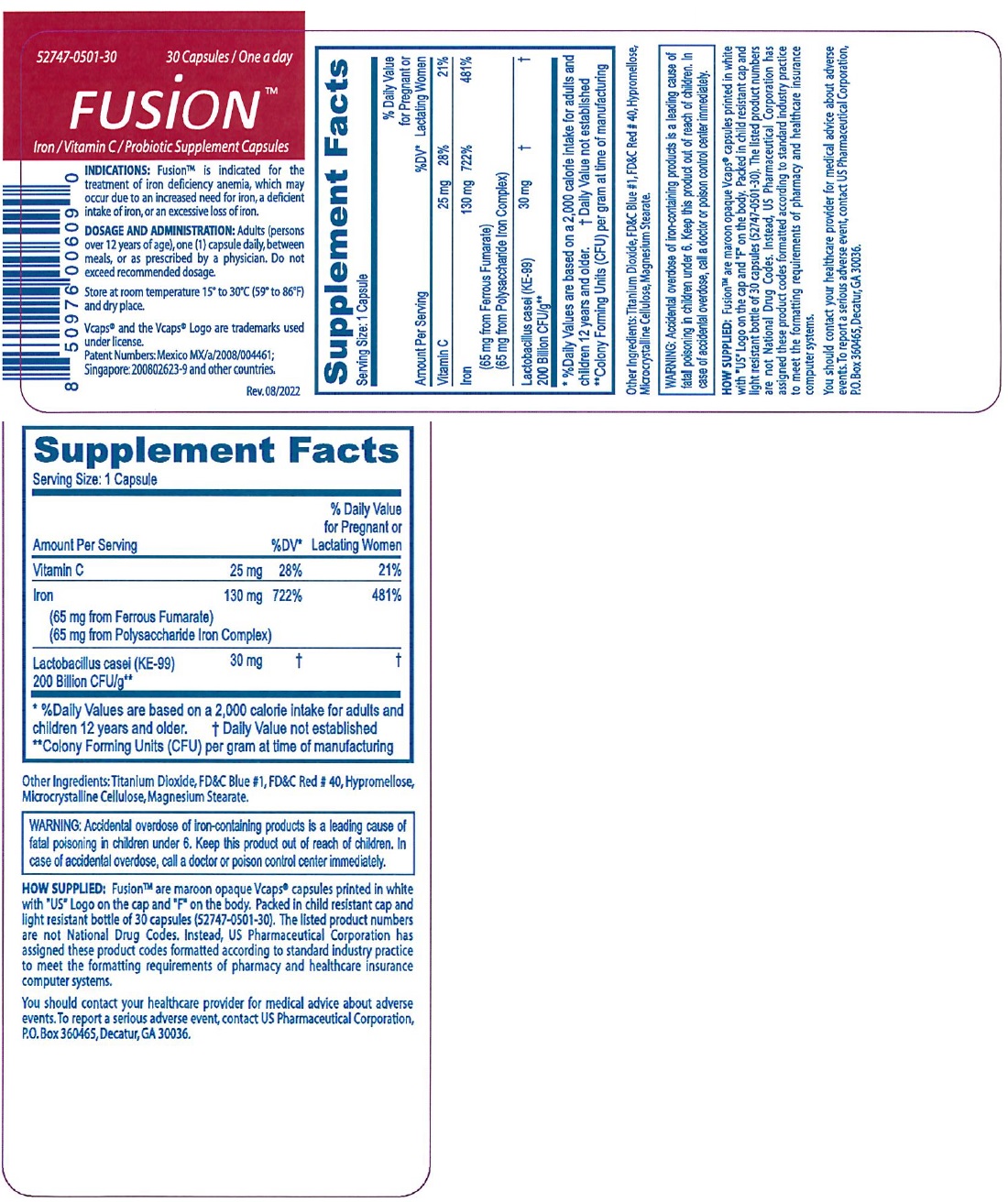 DRUG LABEL: FUSION
NDC: 52747-501 | Form: CAPSULE
Manufacturer: U.S. Pharmaceutical Corporation
Category: other | Type: DIETARY SUPPLEMENT
Date: 20231110

ACTIVE INGREDIENTS: ASCORBIC ACID 25 mg/1 1; FERROUS FUMARATE 65 mg/1 1; IRON POLYMALTOSE 65 mg/1 1; LACTICASEIBACILLUS CASEI 30 mg/1 1
INACTIVE INGREDIENTS: TITANIUM DIOXIDE; FD&C BLUE NO. 1; FD&C RED NO. 40; HYPROMELLOSE, UNSPECIFIED; MICROCRYSTALLINE CELLULOSE; MAGNESIUM STEARATE

FUSIONTM

STATEMENT OF IDENTITY

Supplement Facts
Serving Size: 1 Capsule
Amount Per Serving |  | %DV* | % Daily Value for Pregnant or; Lactating Women
Vitamin C | 25 mg | 28% | 21%
Iron (65 mg from Ferrous Fumarate) (65 mg from Polysaccharide Iron Complex) | 130 mg | 722% | 481%
Lactobacillus casei (KE-99) 200 Billion CFU/g** | 30 mg | † | †
* %Daily Values are based on a 2,000 calorie intake for adults and children 12 years and older. † Daily value not established
** Colony Forming Units (CFU) per gram at time of manufacturing

Other Ingredients: Titanium Dioxide, FD&C Blue #1, FD&C Red # 40, Hypromellose, Microcrystalline Cellulose, Magnesium Stearate.

INDICATIONS: FusionTM is indicated for the treatment of iron deficiency anemia, which may occur due to an increased need for iron, a deficient intake of iron, or an excessive loss of iron.

WARNINGS

WARNING: Accidental overdose of iron-containing products is a leading cause of fatal poisoning in children under 6. Keep this product out of reach of children. In case of accidental overdose, call a doctor or poison control center immediately.

HOW SUPPLIED: FusionTM are maroon opaque Vcaps® capsules printed in white with "US" Logo on the cap and "F" on the body. Packed in child resistant cap and light resistant bottle of 30 capsules (52747-0501-30). The listed product numbers are not National Drug Codes. Instead, US Pharmaceutical Corporation has assigned these product codes formatted according to standard industry practice to meet the formatting requirements of pharmacy and healthcare insurance computer systems.

You should contact your healthcare provider for medical advice about adverse events. To report a serious adverse event, contact US Pharmaceutical Corporation, P.O.Box 360465, Decatur, GA 30036.

DOSAGE AND ADMINISTRATION: Adults (persons over 12 years of age), one (1) capsule daily, between meals, or as prescribed by a physician. Do not exceed recommended dosage.

SAFE HANDLING WARNING

Store at room temperature 15° to 30°C (59° to 86°F) and dry place.

Vcaps® and the Vcaps® Logo are trademarks used under license.

Patent Numbers: Mexico MX/a/2008/004461; Singapore: 200802623-9 and other countries.

Rev. 08/2022

HEALTH CLAIM

Iron / Vitamin C / Probiotic Supplement Capsules